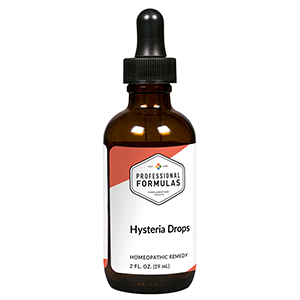 DRUG LABEL: Hysteria Drops
NDC: 63083-2119 | Form: LIQUID
Manufacturer: Professional Complementary Health Formulas
Category: homeopathic | Type: HUMAN OTC DRUG LABEL
Date: 20190815

ACTIVE INGREDIENTS: VALERIAN 2 [hp_X]/59 mL; CASTOR FIBER SCENT GLAND SECRETION 3 [hp_X]/59 mL; PULSATILLA MONTANA WHOLE 4 [hp_X]/59 mL; FERULA ASSA-FOETIDA RESIN 6 [hp_X]/59 mL; ASTERIAS RUBENS 6 [hp_X]/59 mL; STRYCHNOS IGNATII SEED 6 [hp_X]/59 mL; MOSCHUS MOSCHIFERUS MUSK SAC RESIN 6 [hp_X]/59 mL; PICRIC ACID 6 [hp_X]/59 mL; ZINC 6 [hp_X]/59 mL; AVICULARIA AVICULARIA 8 [hp_X]/59 mL; PLATINUM 12 [hp_X]/59 mL
INACTIVE INGREDIENTS: ALCOHOL; WATER

C119

ACTIVE INGREDIENTS

Valeriana officinalis 2X
Castoreum 3X
Pulsatilla 4X
Asafoetida 6X
Asterias rubens 6X
Ignatia amara 6X
Moschus 6X
Picricum acidum 6X
Zincum metallicum 6X
Mygale 8X
Platinum metallicum 12X

QUESTIONS

Professional Formulas

PO Box 2034 Lake Oswego, OR 97035

INDICATIONS

For temporary relief of anxiousness, faintness, irritability, insomnia, or overreaction, particularly with unreasonable fears.*

PURPOSE

*Claims based on traditional homeopathic practice, not accepted medical evidence. Not FDA evaluated.

WARNINGS

In case of overdose, get medical help or contact a poison control center right away.

Keep out of the reach of children.

PREGNANCY OR BREAST FEEDING

If pregnant or breastfeeding, ask a healthcare professional before use.

DIRECTIONS

Place drops under tongue 30 minutes before/after meals. Adults and children 12 years and over: Take 10 drops up to 3 times per day. Consult a physician for use in children under 12 years of age.

OTHER INFORMATION

Tamper resistant. If seal is broken, do not use. After opening, close container tightly and store at room temperature away from heat.

INACTIVE INGREDIENTS

20% ethanol, purified water.

LABEL

Est 1985

Professional Formulas

Complementary Health

Hysteria Drops

Homeopathic Remedy

2 FL. OZ. (59 mL)